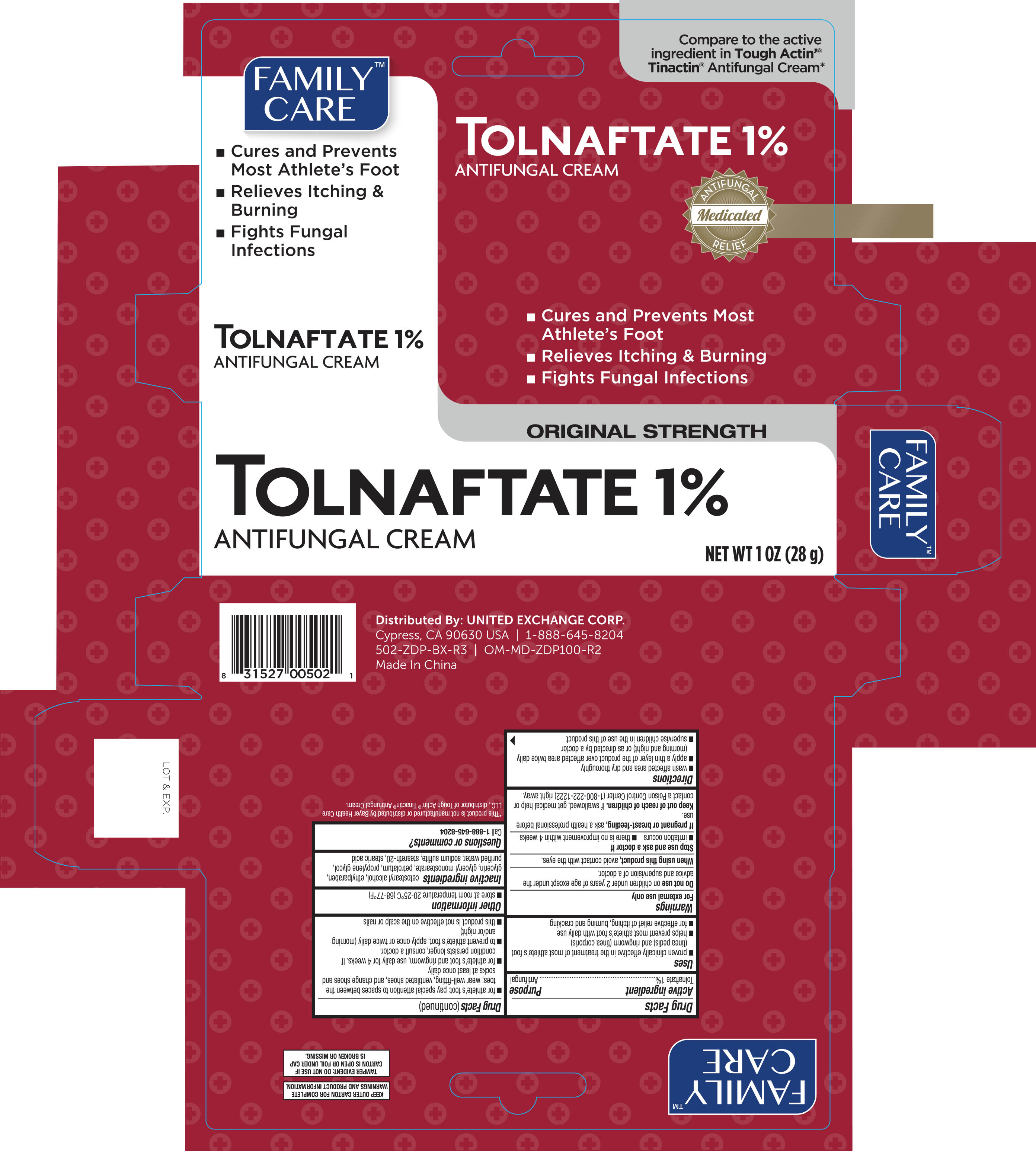 DRUG LABEL: Family Care Antifungal
NDC: 65923-021 | Form: CREAM
Manufacturer: United Exchange Corp.
Category: otc | Type: HUMAN OTC DRUG LABEL
Date: 20251029

ACTIVE INGREDIENTS: TOLNAFTATE 10 mg/1 g
INACTIVE INGREDIENTS: GLYCERYL MONOSTEARATE; PETROLATUM; STEARIC ACID; PROPYLENE GLYCOL; WATER; SODIUM SULFITE; STEARETH-20; GLYCERIN; CETOSTEARYL ALCOHOL; ETHYLPARABEN

Family Care Tolnaftate Cream 1 oz 502

Active ingredient Purpose

Tolnaftate 1%..................................................................Antifungal

Uses

- proven clinically effective in the treatment of most athlete's foot (tinea pedis) and ringworm (tinea corporis)
- helps prevent most athlete's foot with daily use
- for effective relief of itching, burning and cracking

Warnings

For external use only

When using this product avoid contact with the eyes

Stop use and ask a doctor if

- irritation occurs
- there is no improvement within 4 weeks

Do not use on children under 2 years of age except under the advice and supervision of a doctor.

Keep out of reach of children. If swallowed, get medical help or contact a Poison Control Center immediately.

Directions

- wash affected area and dry thoroughly
- apply a thin layer over affected area twice daily (morning and night)
- supervise children in the use of this product
- for athlete's foot: pay special attention to spaces between the toes; well-fitting, ventilated shoes and change shoes and socks at least once daily
- use daily for 4 weeks; if condition persists longer, ask a doctor
- to prevent athlete's foot, apply once or twice daily (morning and/or night)
- this product is not effective on the scalp or nails

Other information

- store between 20° to 25°C (68° to 77°F)
- Lot No. & Exp. Date: see box or see crimp of tube

Inactive ingredients

cetostearly alcohol, ethylparaben, glycerin, light mineral oil, propylene glycol, purified water, sodium sulfite, stearth-20, stearic acid

DOSAGE AND ADMINISTRATION

Distributed by:

United Exchange Corp.

5836 Corporate Ave.

Cypress, CA 90630 USA

1-800-814-8028

Made in China